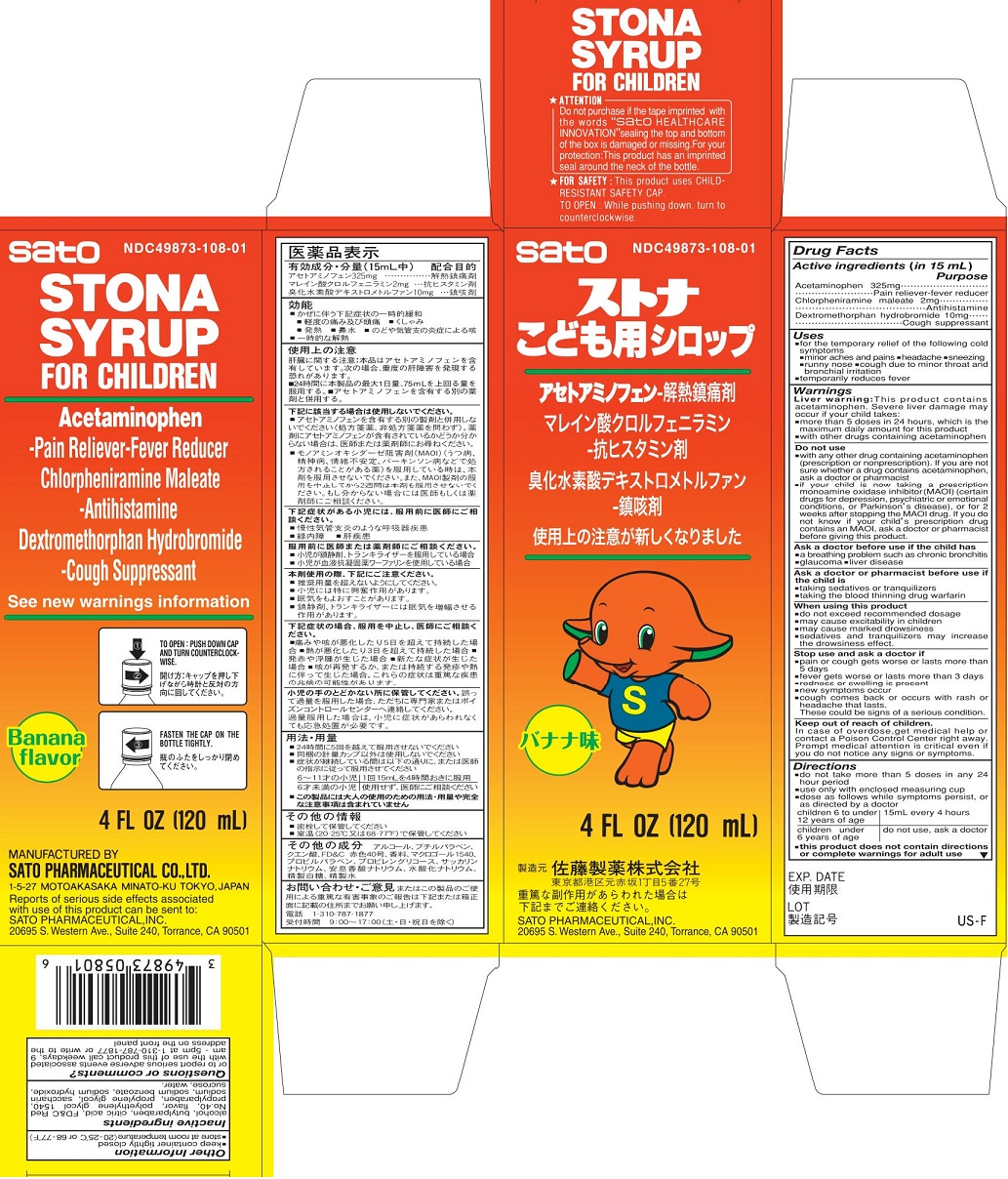 DRUG LABEL: Stona for Children
NDC: 49873-108 | Form: SYRUP
Manufacturer: Sato Pharmaceutical Co., Ltd.
Category: otc | Type: HUMAN OTC DRUG LABEL
Date: 20250119

ACTIVE INGREDIENTS: ACETAMINOPHEN 325 mg/15 mL; CHLORPHENIRAMINE MALEATE 2 mg/15 mL; DEXTROMETHORPHAN HYDROBROMIDE 10 mg/15 mL
INACTIVE INGREDIENTS: BUTYLPARABEN; ALCOHOL; CITRIC ACID MONOHYDRATE; FD&C RED NO. 40; PROPYLPARABEN; PROPYLENE GLYCOL; SODIUM BENZOATE; SODIUM HYDROXIDE; SACCHARIN SODIUM; SUCROSE; WATER; POLYETHYLENE GLYCOL 1500

Stona Syrup for Children (PLD/MFR)

Active ingredients (in 15 mL)
Acetaminophen 325mg
Chlorpheniramine maleate 2mg
Dextromethorphan hydrobromide 10mg

Purpose
Acetaminophen Pain reliever-fever reducer
Chlorpheniramine maleate Antihistamine
Dextromethorphan hydrobromide Cough suppressant

Uses

- For the temporary relief of the following cold symptoms
- minor aches and pains
- headache
- sneezing
- runny nose
- cough due to minor throat and bronchial irritation

- temporarily reduces fever

Warnings

Liver warning: This product contains acetaminophen. Severe liver damage may occur if your child takes:

- more than 5 doses in 24 hours, which is the maximum daily amount for this product
- with other drugs containing acetaminophen

Do not use

- with any other drug containing acetaminophen (prescription or nonprescription). If you are not sure whether a drug contains acetaminophen, ask a doctor or pharmacist.
- if your child is now taking a prescription monoamine oxidase inhibitor (MAOI) (certain drugs for depression, psychiatric or emotional conditions, or Parkinson’s disease), or for 2 weeks after stopping the MAOI drug. If you do not know if your child’s prescription drug contains an MAOI, ask a doctor or pharmacist before giving this product.

Ask a doctor before use if the child has

- a breathing problem such as chronic bronchitis
- glaucoma
- liver disease

Ask a doctor or pharmacist before use if the child is

- taking sedatives or tranquilizers
- taking the blood thinning drug warfarin

When using this product

- do not exceed recommended dosage
- may cause excitability in children
- may cause marked drowsiness
- sedatives and tranquilizers may increase the drowsiness effect

Stop use and ask a doctor if
■pain or cough gets worse or lasts more than 5 days
■fever gets worse or lasts more than 3 days
■redness or swelling is present
■new symptoms occur
■cough comes back or occurs with rash or headache that lasts.
These could be signs of a serious condition.

Keep out of reach of children. In case of overdose, get medical help or contact a Poison Control Center right away. Prompt medical attention is critical even if you do not notice any signs or symptoms.

Directions

- do not take more than 5 doses in any 24 hour period
- use only with enclosed measuring cup
- dose as follows while symptoms persist, or as directed by a doctor

children 6 to under 12 years of age: Take 15 mL every 4 hours

children under 6 years of age: do not use. ask a doctor.

This product does not contain directions or complete warnings for adult use

Other information

- keep container tightly closed
- store at room temperature (20-25 C or 68-77 F)

Inactive ingredients
alcohol, butylparaben, citric acid, FD&C Red No. 40, flavor, polyethylene glycol 1540, propylparaben, propylene glycol, saccharin sodium, sodium benzoate, sodium hydroxide, sucrose, water.

Questions or comments?

or to report serious adverse events associated with the use of this product call weekdays, 9 am - 5 pm at 1-310-787-1877 or write to the address on the front panel